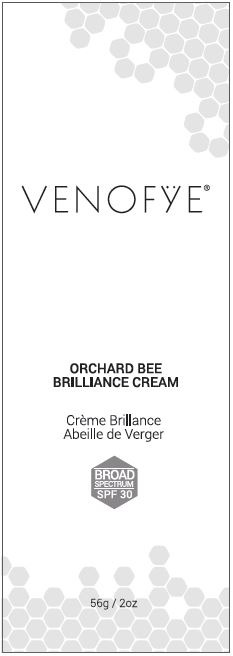 DRUG LABEL: Venofye Orchard Bee Brilliance SPF 30
NDC: 72104-874 | Form: CREAM
Manufacturer: Innovation Brands Inc.
Category: otc | Type: HUMAN OTC DRUG LABEL
Date: 20250710

ACTIVE INGREDIENTS: OCTINOXATE 7.40 g/100 g; HOMOSALATE 6.20 g/100 g; OCTISALATE 5.00 g/100 g; OXYBENZONE 3.10 g/100 g; AVOBENZONE 1.50 g/100 g
INACTIVE INGREDIENTS: WATER; ALKYL (C12-15) BENZOATE; GLYCERIN; GLYCERYL MONOSTEARATE; STEARIC ACID; PEG-100 MONOSTEARATE; TOCOPHEROL; VITAMIN A PALMITATE; ALOE VERA LEAF; GREEN TEA LEAF; SODIUM PYRROLIDONE CARBOXYLATE; APIS MELLIFERA VENOM; POLYSORBATE 60; CARBOMER INTERPOLYMER TYPE A (ALLYL SUCROSE CROSSLINKED); EDETATE DISODIUM; TROLAMINE; PHENOXYETHANOL; ETHYLHEXYLGLYCERIN

VENOFYE® Orchard Bee Brilliance Cream SPF 30

Active Ingredients

Ethylhexyl Methoxycinnamate 7.40%
Homosalate 6.20%
Ethylhexyl Salicylate 5.00%
Benzophenone-3 3.10%
Butyl Methoxydibenzoylmethane 1.50%

Purpose

Sunscreen

Uses

1. Helps prevent sunburn.

Warnings

For external use only. Do not use on damaged or broken skin.

Keep out of eyes. If contact occurs, rinse with water. If rash or irritation develops, discontinue use and consult your physician.

Stop using this product and ask a doctor

if rash or redness develops and lasts.

Keep out of reach of children.

If accidental ingestion, call the Poison Control Center right away.

Directions

1. After cleansing, apply liberally and evenly 15 minutes before sun exposure. Smooth over face and neck and chest daily for optimal results.
2. Reapply at least every two (2) hours.
3. Use water resistant sunscreen if swimming or sweating.

Sun Protection Measures. Spending time in the sun increases your risk of skin cancer and early skin aging. To decrease this risk, regularly use a sunscreen with a Broad Spectrum SPF value of 15 or higher and other sun protection measures including:

1. limit time in the sun, especially from 10 a.m.-2 p.m.
2. wear long-sleeved shirts, pants, hats and sunglasses

For children under 6 months of age: Ask doctor.

Other Information

Protect the product in this container from excessive heat and direct sun. Store at room temperature.

Inactive Ingredients

Aqua, C12-15 Alkyl Benzoate, Glycerin, Glyceryl Stearate, Stearic Acid, PEG-100 Stearate, Tocopherol, Retinyl Palmitate, Aloe Barbadensis Leaf Extract, Camellia Sinensis Extract, Sodium PCA, Bee Venom, Polysorbate 60, Acrylates/C10-30 Alkyl Acrylate Crosspolymer, Carbomer, Disodium EDTA, Triethanolamine, Phenoxyethanol, Ethylhexylglycerin, Fragrance.

Package/Label Principal Display Panel – Carton Label

VENOFŸE®

ORCHARD BEE
BRILLIANCE CREAM

Crème Brilliance
Abeille de Verger

BROAD
SPECTRUM
SPF 30

56g / 2oz

www.venofye.com
19849 Nordhoff Street
Northridge, CA 91324